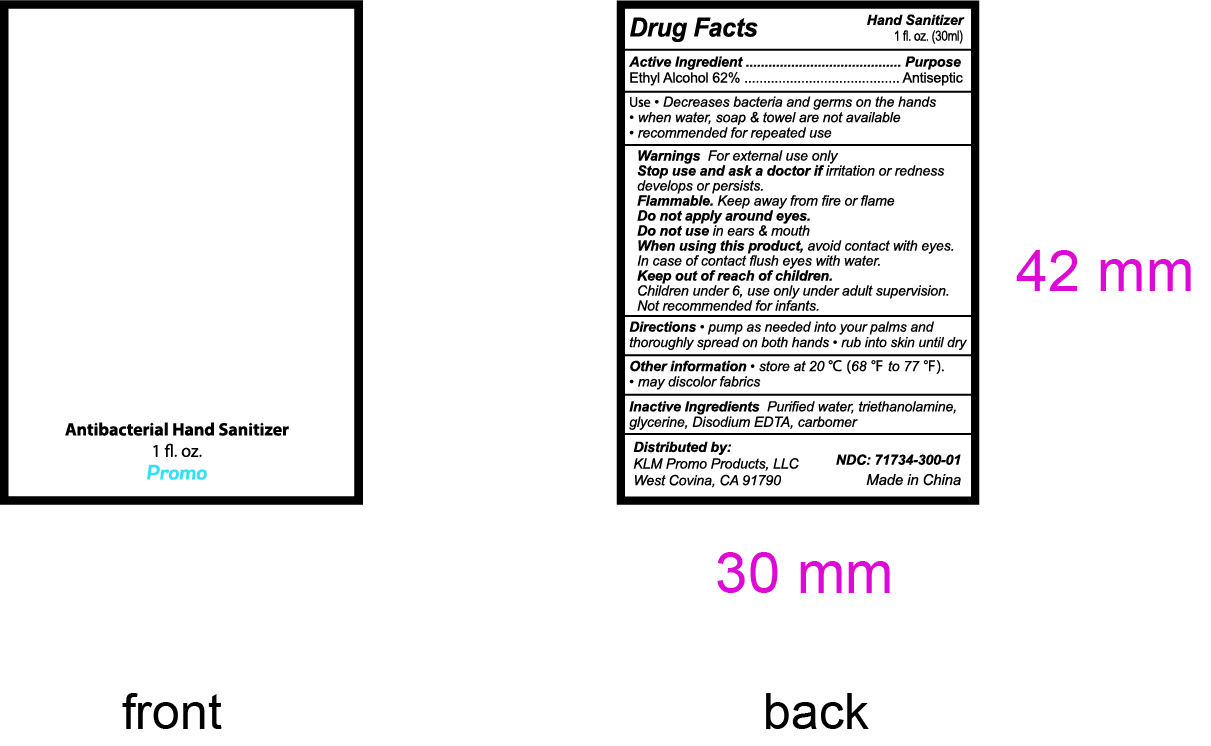 DRUG LABEL: Hand Sanitizer
NDC: 77165-300 | Form: LIQUID
Manufacturer: KLM Promo Products, LLC
Category: otc | Type: HUMAN OTC DRUG LABEL
Date: 20210109

ACTIVE INGREDIENTS: ALCOHOL 62 mL/100 mL
INACTIVE INGREDIENTS: CARBOMER HOMOPOLYMER, UNSPECIFIED TYPE; GLYCERIN; WATER; TROLAMINE; PROPYLENE GLYCOL; EDETATE DISODIUM

klm hand sanitizer

Active Ingredient(s)

Ethyl Alcohol 62%. Purpose: Antiseptic

Purpose

Antiseptic, Hand Sanitizer

Use

Decrease bacteria and germs on the hands
when water, soap, and towel are not available
recommended for repeated use

Warnings

For external use only. Flammable. Keep away from heat or flame

Do not use in ears and mouth

When using this product avoid contact with eyes. In case of contact flush eyes with water.

Stop use and ask a doctor if irritation or redness develops or persists.

KEEP OUT OF REACH OF CHILDREN

Children under 6, use only under adult supervision. Not recommended for infants.

Directions

- pump as needed on to your palms and thoroughly spread on both hands
- rub into skin until dry

Other information

- store at 20℃(68℉-77℉)
- may discolor fabrics

Inactive ingredients

Purified Water, Triethanolamine, Glycerin, Disodium EDTA, Carbomer

Package Label - Principal Display Panel

30 mL NDC: 77165-300-01

antibacterial hand sanitizer

1 fl.oz. (30ml)